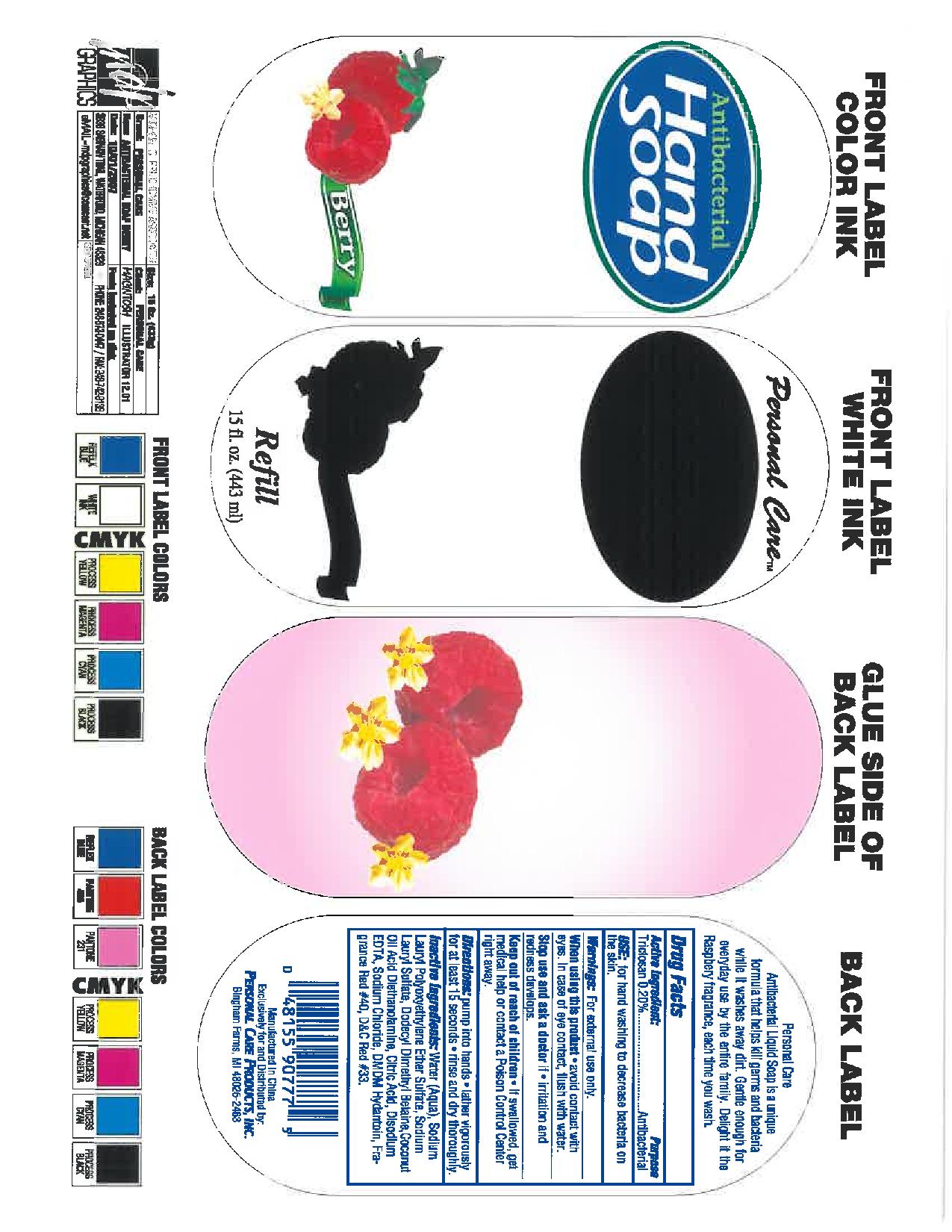 DRUG LABEL: hand
NDC: 29500-907 | Form: SOAP
Manufacturer: Personal Care Products
Category: otc | Type: HUMAN OTC DRUG LABEL
Date: 20110428

ACTIVE INGREDIENTS: TRICLOSAN .888 mL/444 mL
INACTIVE INGREDIENTS: WATER; SODIUM LAURETH SULFATE; SODIUM CHLORIDE; COCO DIETHANOLAMIDE; DMDM HYDANTOIN; CITRIC ACID MONOHYDRATE; EDETATE SODIUM; D&C RED NO. 33

Hand

Active ingredient

.2% triclosan

Purpose antibacterial

Keep out of reach of children.If swallowed get medical help or contact a Poison Control Center right away.

INDICATIONS AND USAGE

Uses for hand washing to decrease bacteria on the skin

Warnings

for external use only

When using this product avoid contact with eyes. In case of eye contact, flush with water.

Stop use and ask a doctor if irritation and redness develops

Directions

Pump into hands

lather vigorously for at least 15 seconds

rinse and dry thoroughly

Inactive ingredients

water (aqua), sodium laureth sulfate, sodium chloride, cocamide DEA, DMDM hydatoin, fragrance, citric acid, tetrasodium EDTA, red#33, red#4

PACKAGE LABEL

Personal care

antibacterial kills 99% of germs

Hand soap

refill

raspberry

15 fl oz (444ml)